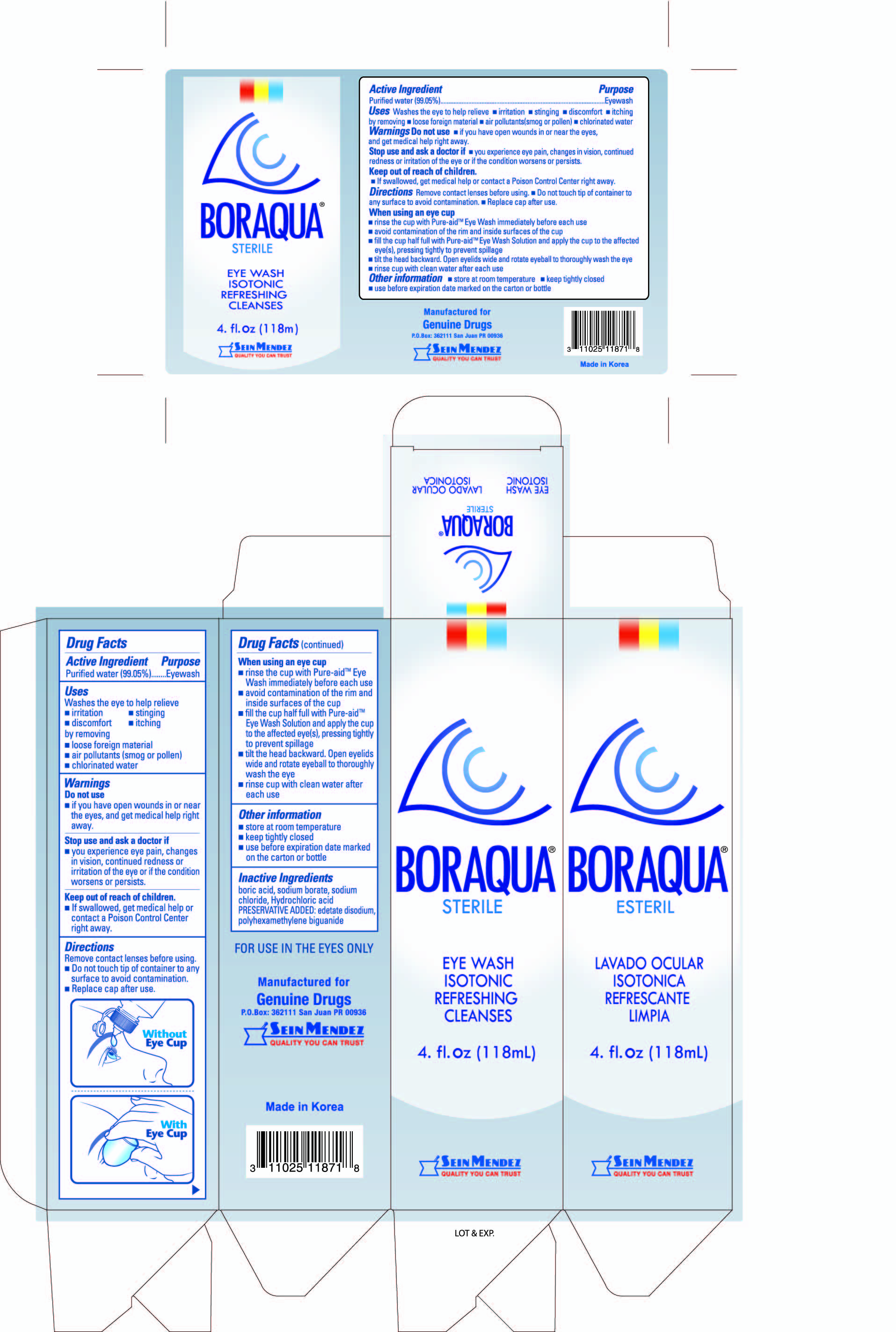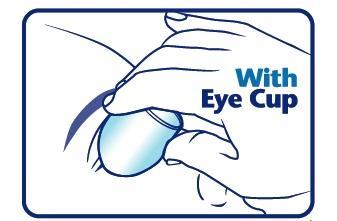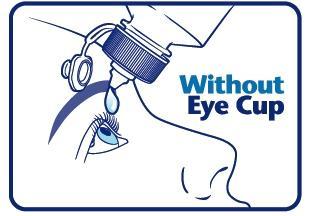 DRUG LABEL: Boraqua Eye Wash
NDC: 69666-187 | Form: SOLUTION
Manufacturer: Genuine Drugs
Category: otc | Type: HUMAN OTC DRUG LABEL
Date: 20240812

ACTIVE INGREDIENTS: WATER 99.05 mL/100 mL
INACTIVE INGREDIENTS: BORIC ACID; SODIUM BORATE; SODIUM CHLORIDE; HYDROCHLORIC ACID; EDETATE DISODIUM; POLYAMINOPROPYL BIGUANIDE

Boraqua Eye Wash

Purpose

Eyewash

Active ingredient

Purified water (99.05%)

Uses

washes the eye to help relieve

- irritation
- stinging
- discomfort
- itching;

by removing

- loose foreign material
- air pollutants (smog or pollen)
- chlorinated water

Warnings

Do not use

- if you have open wounds in or near the eyes, and get medical help right away

Keep out of reach of children.

If swallowed, get medical help or contact a Poison Control Center right away.

Stop use and ask a doctor if

- you experience eye pain, changes in vision, continued redness or irritation of the eye
- condition worsens or persists

Directions

Remove contact lenses before using.

- Do not touch tip of container to any surface to avoid contamination.
- Replace cap after use.

When using an eye cup

- rinse the cup with Pure-aid Eye Wash immediately before each use
- avoid contamination of the rim and inside surfaces of the cup
- fill the cup half full with Pure-aid Eye Wash Solution and apply the cup to the affected eye(s), pressing tightly to prevent spillage
- tilt the head backward. Open eyelids wide and rotate eyeball to thoroughly wash the eye
- rinse cup with clean water after each use

Other information

- store at room temperature
- keep tightly closed
- use before expiration date marked on the carton or bottle

Inactive ingredients

boric acid, sodium borate, sodium chloride, Hydrochloric acid PRESERVATIVE ADDED: edetate disodium, polyhexamethylene biguanide

PACKAGE LABEL

Boraqua